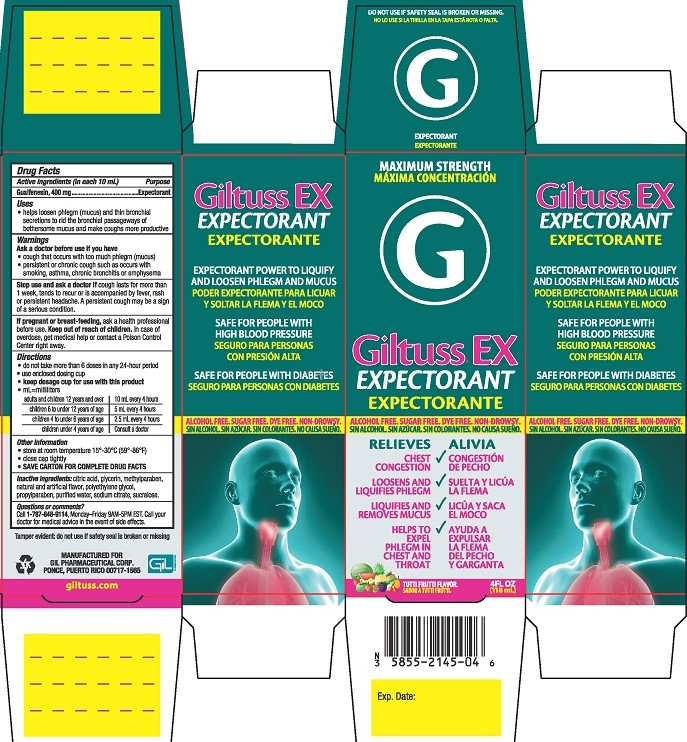 DRUG LABEL: Giltuss EX Expectorant
NDC: 58552-145 | Form: SOLUTION
Manufacturer: Gil Pharmaceutical Corp
Category: otc | Type: HUMAN OTC DRUG LABEL
Date: 20251009

ACTIVE INGREDIENTS: GUAIFENESIN 400 mg/10 mL
INACTIVE INGREDIENTS: POLYETHYLENE GLYCOL, UNSPECIFIED; SODIUM CITRATE; WATER; GLYCERIN; SUCRALOSE; ANHYDROUS CITRIC ACID; METHYLPARABEN; PROPYLPARABEN

Giltuss EX Expectorant

Drug Facts

Active ingredient (in each 10 mL)

Guaifenesin, 400 mg

Purpose

Expectorant

Uses

- helps loosen phlegm (mucus) and thin bronchial secretions to rid the bronchial passageways of bothersome mucus and make coughs more productive

Warnings

Ask a doctor before use if you have

- cough that occurs with too much phlegm (mucus)
- persistent or chronic cough such as occurs with smoking, asthma, chronic bronchitis, or emphysema

Stop use and ask a doctor ifcough lasts for more than 1 week, tends to recur, or is accompanied by fever, rash or persistent headache. A persistent cough may be a sign of a serious condition.

PREGNANCY OR BREAST FEEDING

If pregnant or breast-feeding, ask a health professional before use.

Keep out of reach of children.In case of overdose, get medical help or contact a Poison Control Center right away.

Directions

- do not take more than 6 doses in any 24-hour period
- use enclosed dosing cup
- keep dosage cup for use with this product
- ml = milliliters
  adults and children 12 years and over | 10 mL every 4 hours
  children 6 to under 12 years of age | 5 mL every 4 hours
  children 4 to under 6 years of age | 2.5 mL every 4 hours
  children under 4 years of age | Consult a doctor

Other information

- store at room temperature 15°-30°C (59°-86°F)
- close cap tightly
- SAVE CARTON FOR COMPLETE DRUG FACTS

INACTIVE INGREDIENT

Inactive ingredientscitric acid, glycerin, methylparaben. natural and artificial flavor, polyethylene glycol, propylparaben, purified water, sodium citrate, sucralose.

Questions or comments?Call 1-787-848-9114, Monday-Friday 9AM - 5PM EST. Call your doctor for medical advice in the event of side effects.

Tamper Evident: do not use if safety seal is broken or missing.

MANUFACTURED FOR

GIL PHARMACEUTICAL CORP.

PONCE, PUERTO RICO 00717-1565

giltuss.com

PACKAGE LABEL

MAXIMUM STRENGTH

Giltuss® EX EXPECTORANT

ALCOHOL FREE. SUGAR FREE. DYE FREE. NON-DROWSY

RELIEVES

CHEST CONGESTION

LOOSENS AND LIQUIFIES PHLEGM

LIQUIFIES AND REMOVE MUCUS

HELPS TO EXPEL PHLEGM IN CHEST AND THROAT

TUTTI FRUTTI FLAVOR

4FL OZ (118 mL)